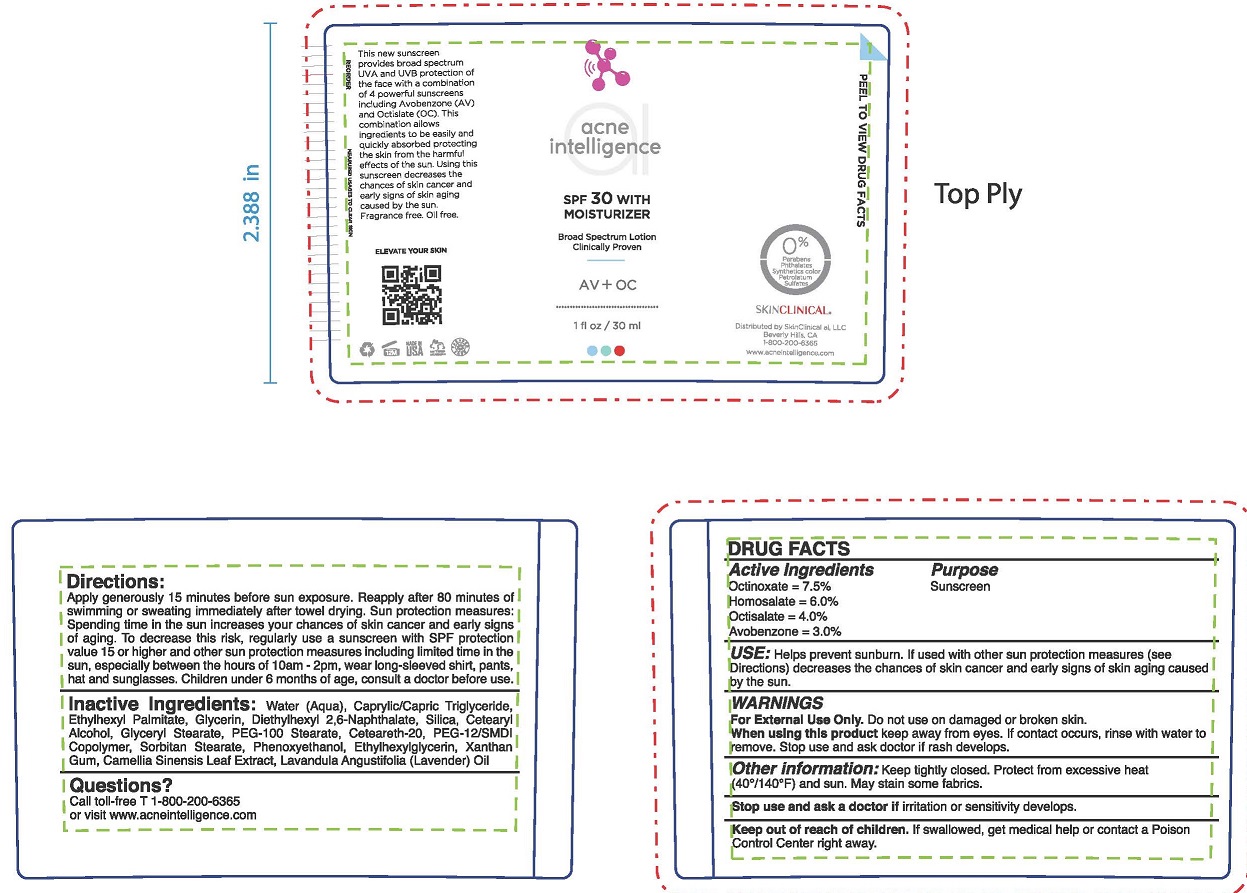 DRUG LABEL: SUNSCREEN WITH MOISTURIZER
NDC: 73110-106 | Form: LOTION
Manufacturer: SkinClinical AI, LLC
Category: otc | Type: HUMAN OTC DRUG LABEL
Date: 20190629

ACTIVE INGREDIENTS: HOMOSALATE 6 g/100 mL; OCTINOXATE 7.5 g/100 mL; OCTISALATE 4 g/100 mL; AVOBENZONE 3 g/100 mL
INACTIVE INGREDIENTS: WATER; MEDIUM-CHAIN TRIGLYCERIDES; ETHYLHEXYL PALMITATE; GLYCERIN; DIETHYLHEXYL 2,6-NAPHTHALATE; SILICON DIOXIDE; CETOSTEARYL ALCOHOL; GLYCERYL MONOSTEARATE; PEG-100 STEARATE; POLYOXYL 20 CETOSTEARYL ETHER; POLYETHYLENE GLYCOL 600; SORBITAN MONOSTEARATE; PHENOXYETHANOL; ETHYLHEXYLGLYCERIN; XANTHAN GUM; GREEN TEA LEAF; LAVENDER OIL

SUNSCREEN SPF-30 WITH MOISTURIZER

ACTIVE INGREDIENTS

OCTINOXATE 7.5%

HOMOSALATE 6.0%

oCTISALATE 4.0%

aVOBENZONE 3.0%

PURPOSE

SUNSCREEN

USE

Helps prevent sunburn. If used with other sun protection measures (see Directions) decreases the chances of skin cancer and early signs of skin aging caused by the sun.

Warnings

For External Use Only. Do not use on damaged or broken skin.

When using this product keep away from eyes. If contact occurs, rinse with water to remove. Stop use and ask doctor if rash develops.

OTHER INFORMATION

Keep tightly closed. Protect from excessive heat (40°/140°F) and sun. May stain some fabrics.

Stop use and ask a doctor if irritation or sensitivity develops.

Keep out of reach of children. If swallowed, get medical help or contact a Poison Control Center right away.

DIRECTIONS

Apply generously 15 minutes before sun exposure. Reapply after 80 minutes of swimming or sweating immediately after towel drying. Sun protection measures: Spending time in the sun increases your chances of skin cancer and early signs of aging. To decrease this risk, regularly use a sunscreen with SPF protection value 15 or higher and other sun protection measures including limited time in the sun, especially between the hours of 10am -2pm, wear long-sleeved shirt, pants, hat and sunglasses. Children under 6 months of age, consult a doctor before use.

Inactive Ingredients

Water (Aqua), Caprylic/Capric Triglyceride, Ethylhexyl Palmitate, Glycerin, Diethylhexyl 2,6-Naphthalate, Silica, Cetearyl Alcohol, Glyceryl Stearate, PEG-100 Stearate, Ceteareth-20, PEG-12/SMDI Copolymer, Sorbitan Stearate, Phenoxyethanol, Ethylhexylglycerin, Xanthan Gum, Camellia Sinensis Leaf Extract, Lavandula Angustifolia (Lavender) Oil

Questions?

CALL TOLL-FREE T 1-800-200-6365

VISIT WWW.ACNEINTELLIGENCE.COM